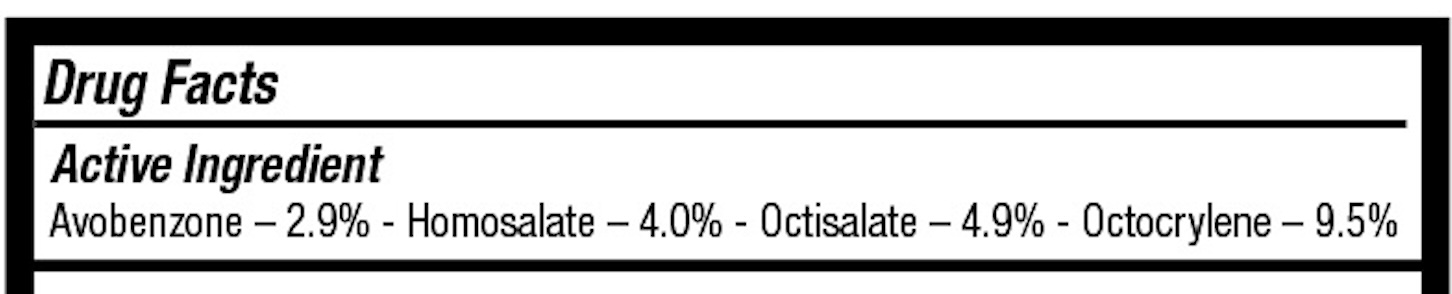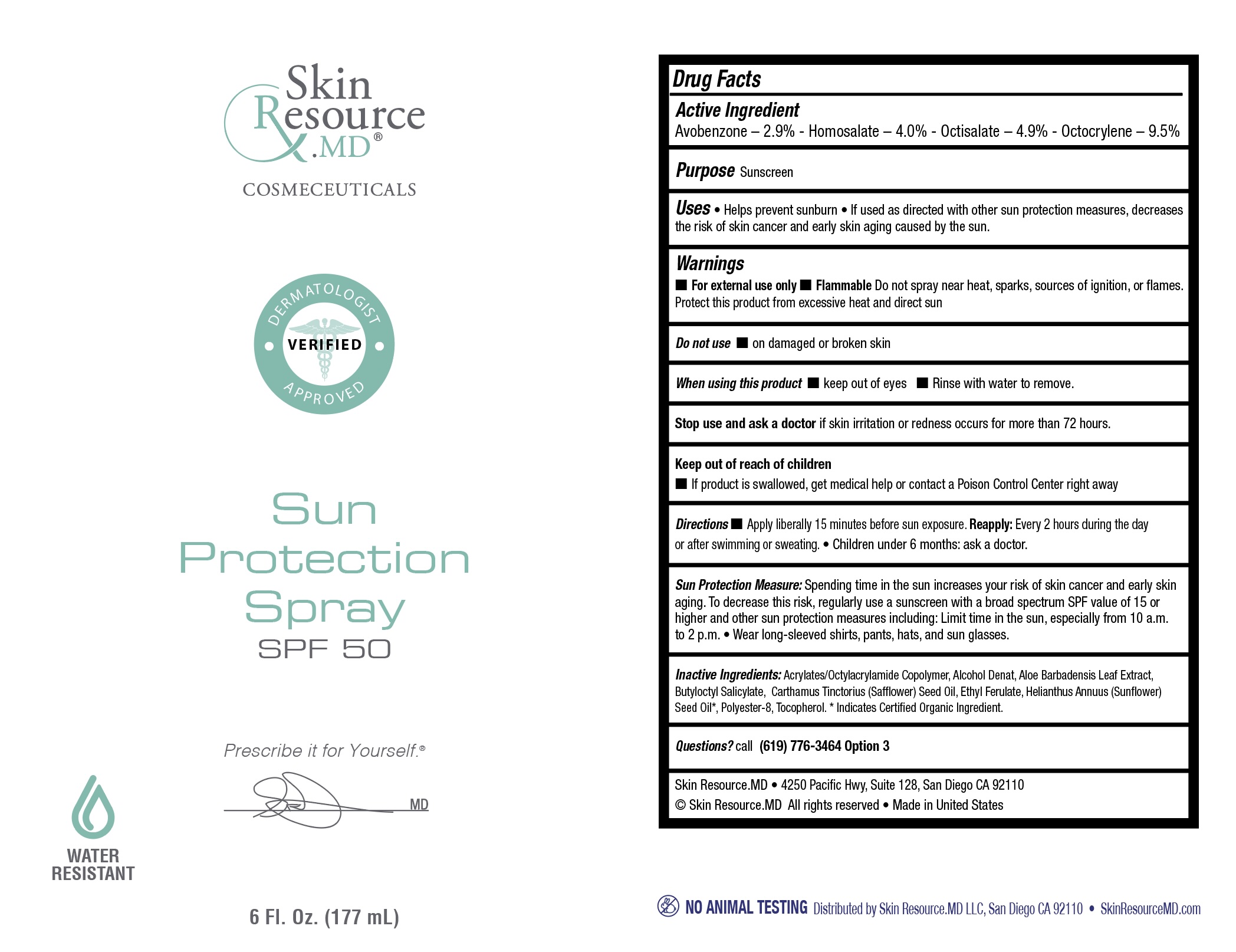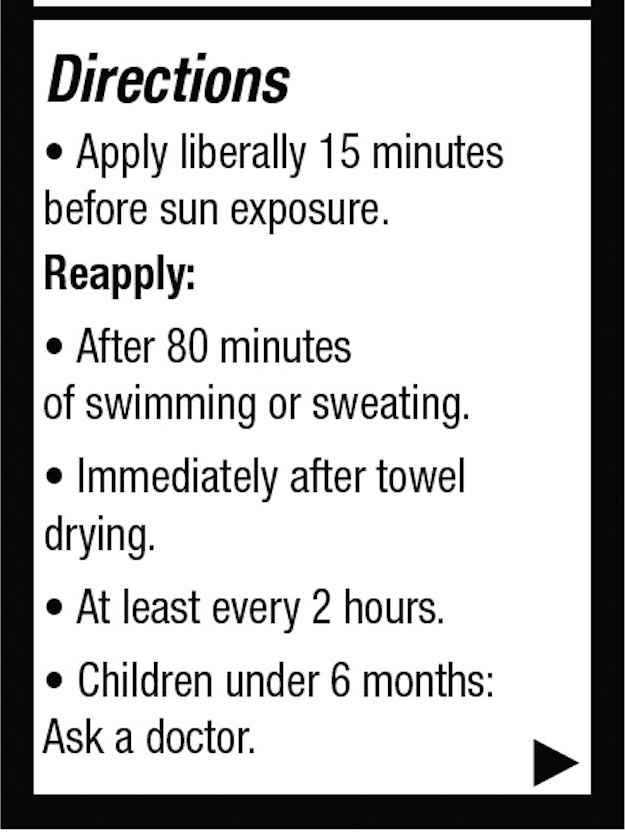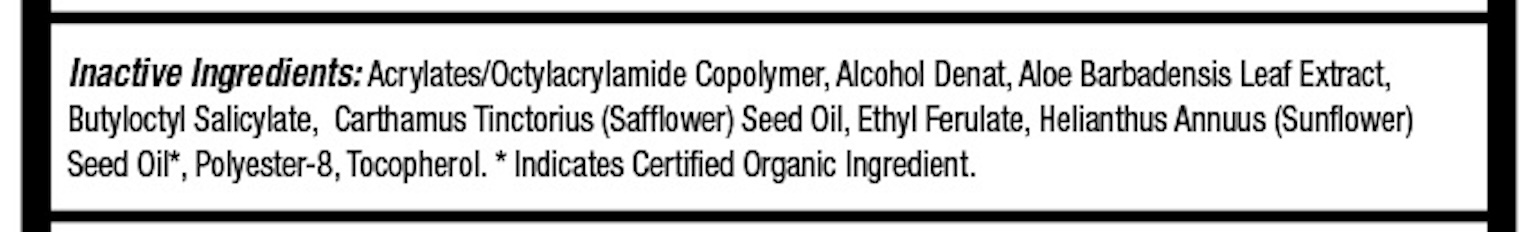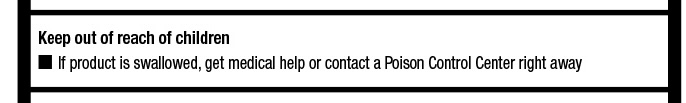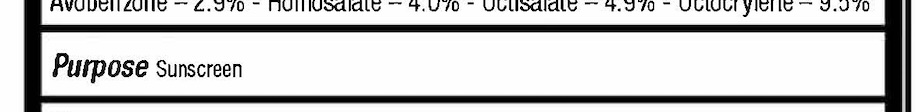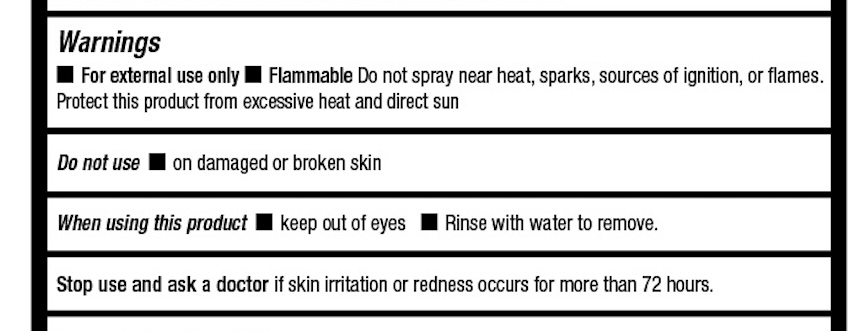 DRUG LABEL: Sun Protection SPF 50
NDC: 83694-011 | Form: SPRAY
Manufacturer: Skinresource.md, L.L.C.
Category: otc | Type: HUMAN OTC DRUG LABEL
Date: 20250625

ACTIVE INGREDIENTS: HOMOSALATE 7.08 g/177 g; OCTOCRYLENE 16.815 g/177 g; OCTISALATE 8.673 g/177 g; AVOBENZONE 5.133 g/177 g
INACTIVE INGREDIENTS: ETHYL FERULATE; ALOE BARBADENSIS LEAF; HELIANTHUS ANNUUS (SUNFLOWER) SEED OIL; DEHYDRATED ALCOHOL; POLYESTER-8 (1400 MW, CYANODIPHENYLPROPENOYL CAPPED); TOCOPHEROL; ACRYLATES/OCTYLACRYLAMIDE COPOLYMER (75000 MW); BUTYLOCTYL SALICYLATE; CARTHAMUS TINCTORIUS (SAFFLOWER) SEED OIL

Active Ingredient

Avobenzone - 2.9% - Homosalate - 4.0% - Octisalate - 4.9% - Octocrylene - 9.5%

Inactive Ingredients:
Acrylates/Octylacrylamide Copolymer, Alcohol Denat, Aloe Barbadensis Leaf Extract, Butyloctyl Salicylate, Carthamus Tinctorius (Safflower) Seed Oil, Ethyl Ferulate, Helianthus Annuus (Sunflower)

Seed Oil*, Polyester-8, Tocopherol.
* Indicates Certified Organic Ingredient.

Keep out of reach of children:

if product is swallowed, get medical help or contact a Poison Control Center right away

Warnings

For external use only Flammable Do not spray near heat, sparks, sources of ignition, or flames.

Protect this product from excessive heat and direct sun

Do not use on damaged or broken skin
When using this product keep out of eyes Rinse with water to remove.
Stop use and ask a doctor if skin irritation or redness occurs for more than 72 hours.

DOSAGE AND ADMINISTRATION

Directions • Apply liberally 15 minutes before sun exposure. Reapply: Every 2 hours during the day or after swimming or sweating. • Children under 6 months: ask a doctor.

Sun Protection Measure: Spending time in the sun increases your risk of skin cancer and early skin aging. To decrease this risk, regularly use a sunscreen with a broad spectrum SPF value of 15 or higher and other sun protection measures including: Limit time in the sun, especially from 10 a.m.

to 2 p.m. • Wear long-sleeved shirts, pants, hats, and sun glasses.

INDICATIONS AND USAGE

Uses • Helps prevent sunburn • If used as directed with other sun protection measures, decreases the risk of skin cancer and early skin aging caused by the sun.

Warnings

• For external use only Flammable Do not spray near heat, sparks, sources of ignition, or flames.

Protect this product from excessive heat and direct sun

Do not use on damaged or broken skin

When using this product keep out of eyes • Rinse with water to remove.

Stop use and ask a doctor if skin irritation or redness occurs for more than 72 hours.

Keep out of reach of children

If product is swallowed, get medical help or contact a Poison Control Center right away

Directions • Apply liberally 15 minutes before sun exposure. Reapply: Every 2 hours during the day after swimming or sweating. • Children under 6 months: ask a doctor.

Sun Protection Measure: Spending time in the sun increases your risk of skin cancer and early skin aging. To decrease this risk, regularly use a sunscreen with a broad spectrum SPF value of 15 or higher and other sun protection measures including: Limit time in the sun, especially from 10 a.m.